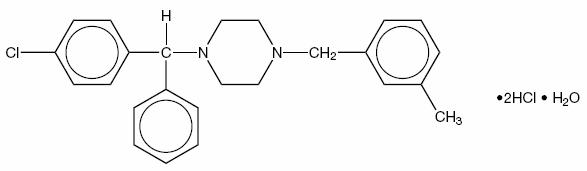 DRUG LABEL: Unknown
Manufacturer: Watson Laboratories, Inc.
Category: prescription | Type: HUMAN PRESCRIPTION DRUG LABELING
Date: 20060328

70010599
Meclizine HCI
Tablets USP
Rx only

DESCRIPTION

Meclizine HCl, an oral antiemetic, is a white, slightly yellowish, crystalline powder which has a slight odor and is tasteless. It has the following structural formula:

C25H27CIN2.2HCl.H2O 481.89

The chemical name is 1-(p-chloro-α-phenylbenzyl)-4-(m-methylbenzyl) piperazine dihydrochloride monohydrate.

Each tablet, for oral administration, contains 12.5 mg or 25 mg of Meclizine HCl. In addition, each tablet contains the following inactive ingredients: colloidal silicon dioxide, corn starch, D&C yellow # 10 lake (25 mg only), FD&C blue # 1 lake (12.5 mg only), lactose monohydrate, microcrystalline cellulose, povidone (12.5 mg only), sodium starch glycolate, and stearic acid.

ACTIONS

Meclizine HCl is an antihistamine which shows marked protective activity against nebulized histamine and lethal doses of intravenously injected histamine in guinea pigs. It has a marked effect in blocking the vasodepressor response to histamine, but only a slight blocking action against acetylcholine. Its activity is relatively weak in inhibiting the spasmogenic action of histamine on isolated guinea pig ileum. It has a slower onset and longer duration of action (24 hours) than most other antihistamines used for motion sickness.

Antihistamines have been observed to have both stimulant and depressant effects on the CNS, but no clear explanation exists in regard to their diverse central actions. The site and mode of their central action is unknown.

INDICATIONS:

Prophylactic treatment and management of nausea and vomiting, and dizziness associated with motion sickness.

CONTRAINDICATIONS

Meclizine HCl is contraindicated in individuals who have shown a previous hypersensitivity to it.

WARNINGS

Some drowsiness may, on occasion, occur with the use of this drug, patients should be warned of this possibility and cautioned against driving a car or operating dangerous machinery.

Patients should avoid alcoholic beverages while taking this drug. Due to its potential anticholinergic action, this drug should be used with caution in patients with asthma, glaucoma, or enlargement of the prostate gland.

USAGE IN PEDIATRIC PATIENTS

Clinical studies establishing safety and effectiveness in pediatric patients have not been done; therefore, usage is not recommended in pediatric patients under 12 years of age.

USAGE IN PREGNANCY

Pregnancy Category B. Reproduction studies in rats have shown cleft palates at 25-50 times the human dose. Epidemiological studies in pregnant women, however, do not indicate that meclizine increases the risk of abnormalities when administered during pregnancy. Despite the animal findings, it would appear that the possibility of fetal harm is remote. Nevertheless, meclizine, or any other medication, should be used during pregnancy only if clearly necessary.

ADVERSE REACTIONS

Drowsiness, dry mouth, and on rare occasions, blurred vision have been reported.

DOSAGE AND ADMINISTRATION

Motion Sickness: The initial dose of 25 to 50 mg of meclizine, should be taken prior to travel for protection against motion sickness. Thereafter, the dose may be repeated every 24 hours for the duration of the journey.

HOW SUPPLIED

Meclizine HCl Tablets USP are supplied as follows:

12.5 mg: Blue/white, oval, bi-layer tablet debossed WATSON and 802 on one side and a partial bisect on the other side, in bottles of 100.

25 mg: Yellow/white, oval, bi-layer tablet debossed WATSON and 803 on one side and a partial bisect on the other side, in bottles of 100 and 1000.

Store at controlled room temperature 15°-30°C (59°- 86°F). Dispense in a well-closed container as defined in USP/NF.

Manufactured For:
Watson Laboratories, Inc.
Corona, CA 92880 USA

Manufactured by:
Patheon Pharmaceuticals Inc.
Cincinnati, OH 45215 USA

Rev. 10/03
70010599